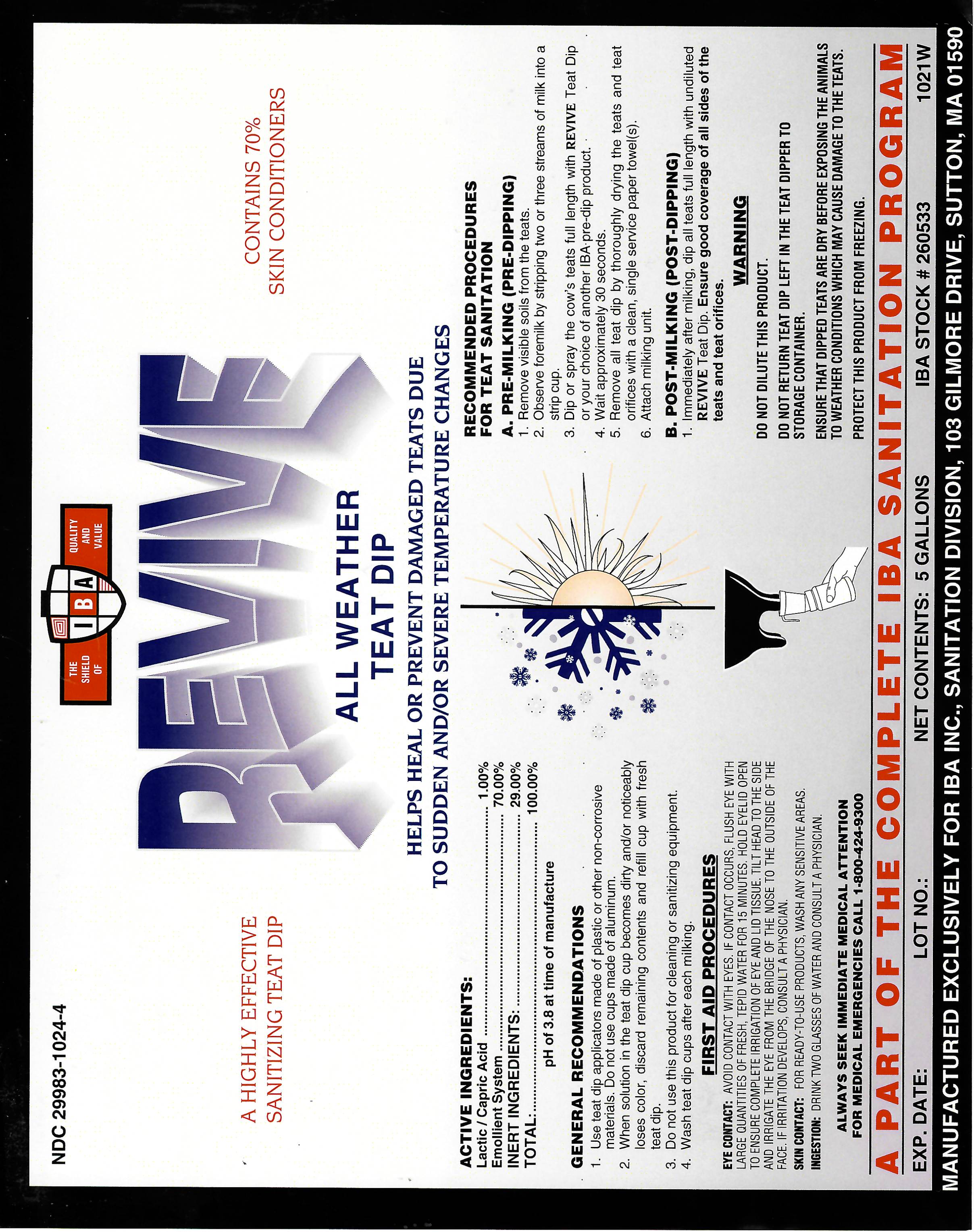 DRUG LABEL: REVIVE
NDC: 29983-1024 | Form: LIQUID
Manufacturer: IBA
Category: animal | Type: OTC ANIMAL DRUG LABEL
Date: 20251211

ACTIVE INGREDIENTS: LACTIC ACID .60 kg/100 kg; CAPRIC ACID .40 kg/100 kg

Revive

ACTIVE INGREDIENT

LACTIC/CAPRIC ACID...........1.0%
EMOLLIENT SYSTEM..............70%

INERT INGREDIENTS

INERT INGREDIENTS.............29%
TOTAL................................100%
pH OF 3.8 AT TIME OF MANUFACTURE

INDICATIONS AND USAGE

GENERAL RECOMMENDATIONS
1. Use teat dip applicators made of plastic or other non-corrosive materials. Do not use cups made of aluminum.
2. When solution in the teat dip cup becomes dirty and/or noticeably loses color, discard remaining contents and refill cup with fresh teat dip.
3. Do not use this product for cleaning or sanitizing equipment
4. Wash Teat Dip cups after each milking.
RECOMMENDED PROCEDURES FOR TEAT SANITATION
A. PRE-MILKING (PRE-DIPPING)
1. REMOVE VISIBLE SOILS FROM THE TEATS.
2. OBSERVE FOREMILK BY STRIPPING TWO OR THREE STREAMS OF MILK INTO A STRIP CUP.
3. DIP OR SPRAY THE COW'S TEATS FULL LENGTH WITH Revive TEAT DIP or your choice if another IBA Pre-dip product..
4. WAIT APPROXIMATELY 30 SECONDS.
5. REMOVE ALL TEAT DIP BY THOROUGHLY DRYING THE TEATS AND TEAT ORIFICES WITH A CLEAN, SINGLE SERVICE PAPER TOWEL(S).
6. ATTACH MILKING UNIT
B.POST-MILKING (POST DIPPING)
Immediately after milking dip all teats full length with REVIVE Teat Dip Ensure good coverage of all sides of the teats and teat orifices.

WARNING

DO NOT DILUTE THIS PRODUCT
DO NOT RETURN TEAT DIP LEFT IN THE TEAT DIPPER TO STORAGE CONTAINER
ENSURE THAT DIPPED TEATS ARE DRY BEFORE EXPOSING THE ANIMALS TO WEATHER CONDITIONS WHICH MAY CAUSE DAMAGE TO THE TEATS.
PROTECT THIS PRODUCT FROM FREEZING.

CAUTION: KEEP OUT OF REACH OF CHILDREN.
AVOID CONTACT WITH FOOD. DO NOT TAKE INTERNALLY.

FIRST AID PROCEDURES

EYE CONTACT: IMMEDIATELY FLUSH EYE WITH LARGE AMOUNTS OF FRESH, TEPID WATER FOR 15 MINUTES. HOLD EYELID OPEN TO ENSURE COMPLETE IRRIGATION OF EYE AND LID TISSUES. TILT HEAD TO THE SIDE AND IRRIGATE THE EYE FROM THE BRIDGE OF THE NOSE TO THE OUTSIDE OF THE FACE.
SKIN CONTACT: WASH ANY SENSITIVE AREAS.
INGESTION: DO NOT INDUCE VOMITING. NEVER GIVE ANYTHING BY MOUTH TO AN UNCONSCIOUS PERSON. DRINK LARGE AMOUNTS OF WATER. IF VOMITING OCCURS KEEP AIRWAYS OPEN. KEEP HEAD LOWER THAN THE HIPS TO PREVENT ASPIRATION INTO THE LUNGS.

ALWAYS SEEK IMMEDIATE MEDICAL ATTENTION FOR MEDICAL EMERGENCIES CALL 1-800-424-9300